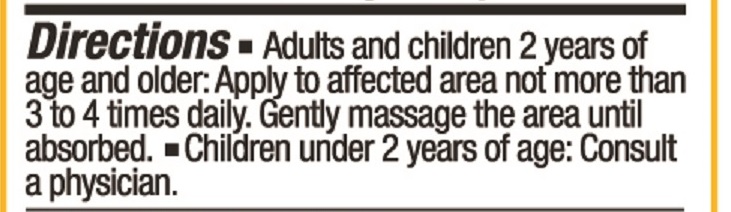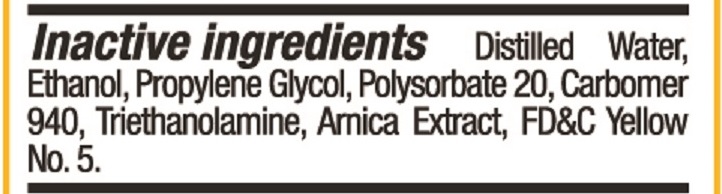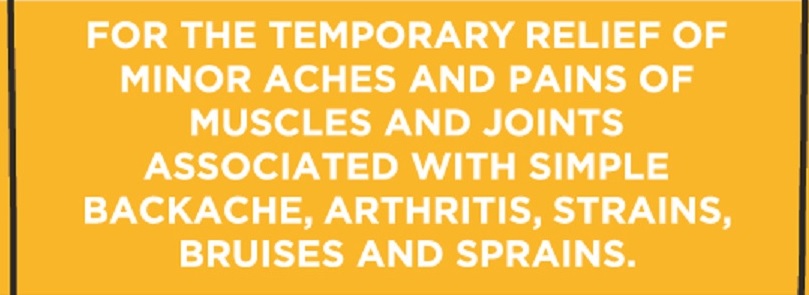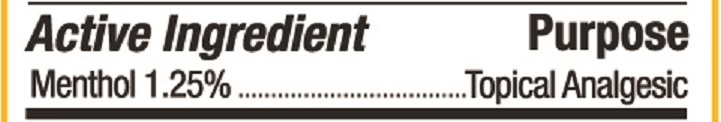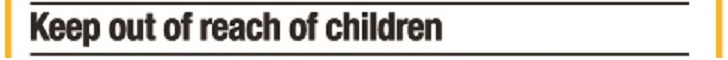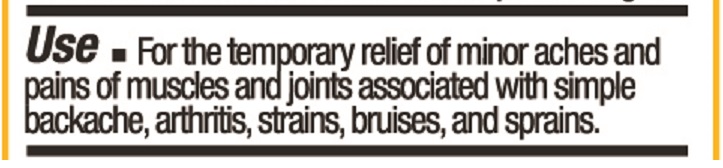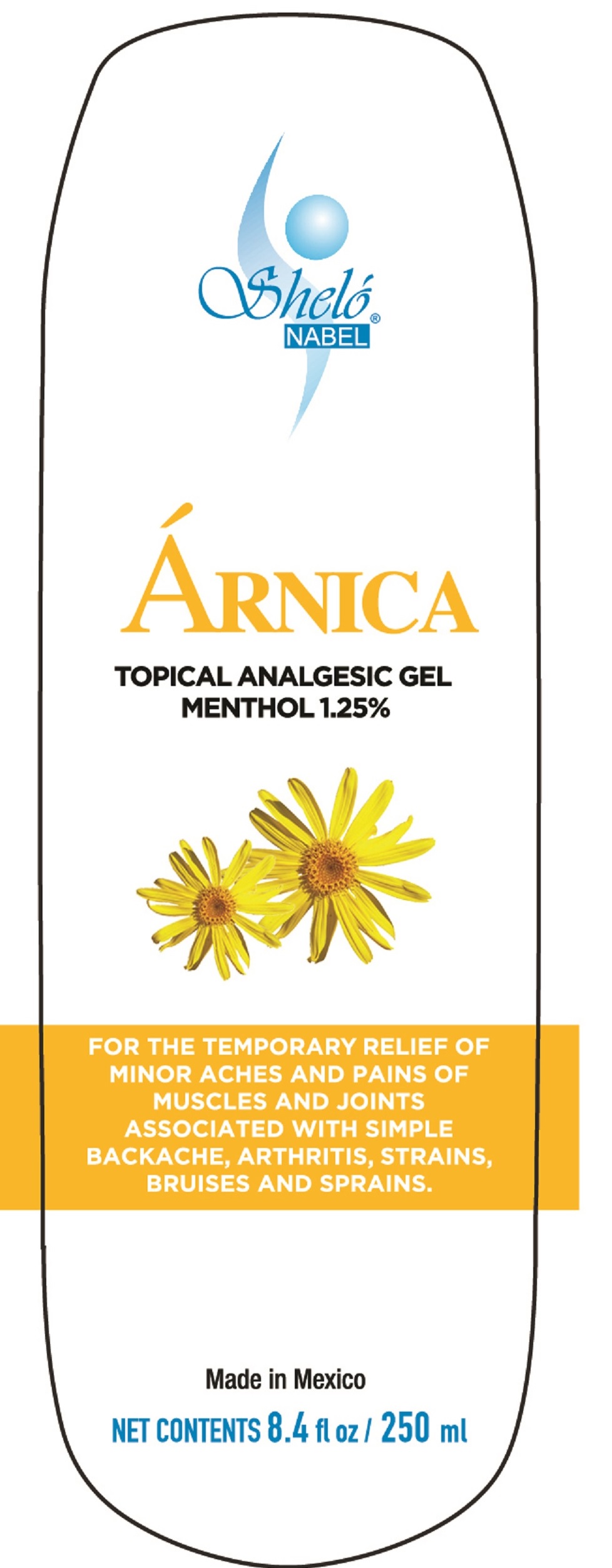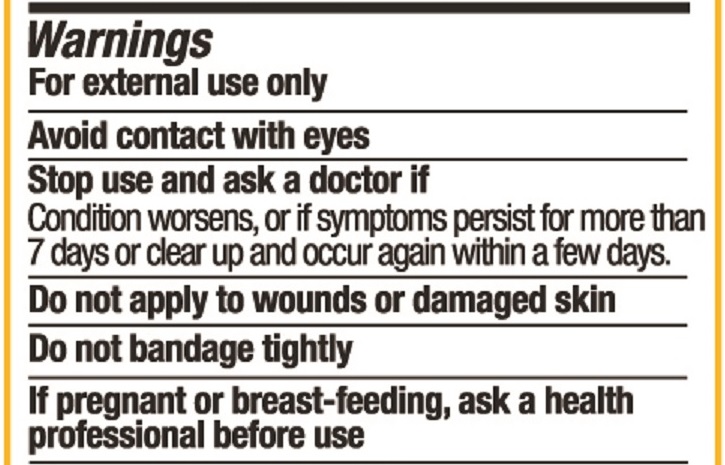 DRUG LABEL: Shelo NABEL Arnica Gel
NDC: 71424-1058 | Form: GEL
Manufacturer: Corporativo Serysi S de R L de C V
Category: otc | Type: HUMAN OTC DRUG LABEL
Date: 20191015

ACTIVE INGREDIENTS: MENTHOL 12.5 mg/1 g
INACTIVE INGREDIENTS: POLYSORBATE 20

Sheló NABEL Árnica Gel